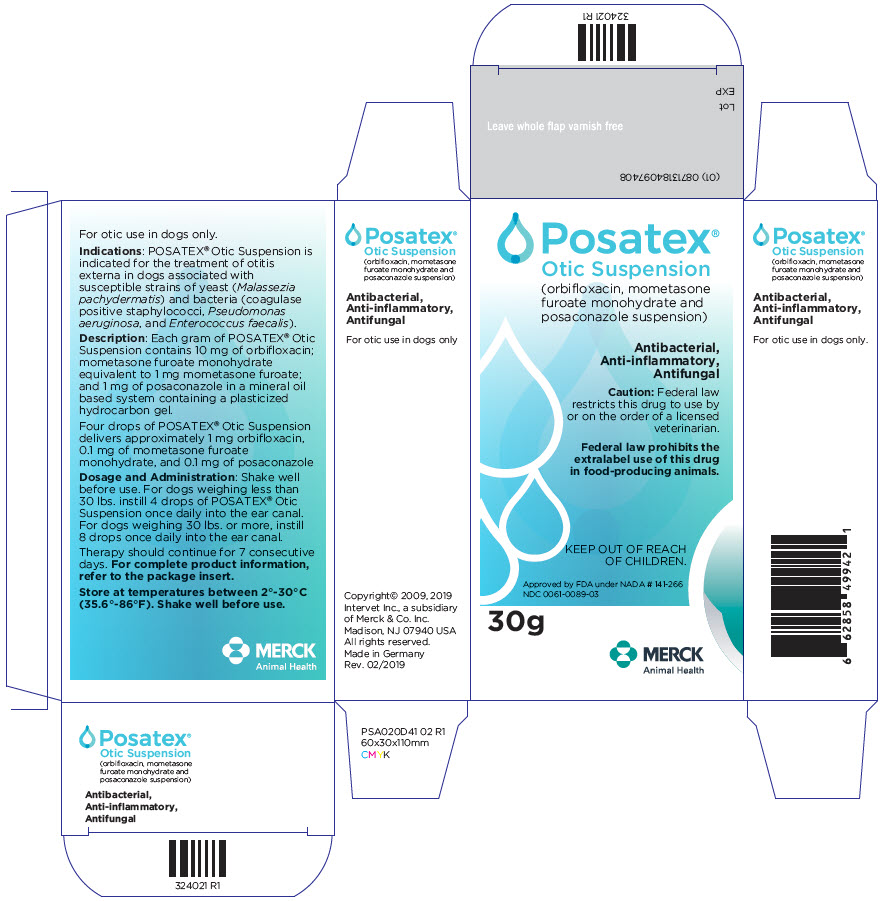 DRUG LABEL: Posatex
NDC: 0061-0089 | Form: SUSPENSION
Manufacturer: Merck Sharp & Dohme Corp.
Category: animal | Type: PRESCRIPTION ANIMAL DRUG LABEL
Date: 20241029

ACTIVE INGREDIENTS: ORBIFLOXACIN 10 mg/1 g; MOMETASONE FUROATE 1 mg/1 g; POSACONAZOLE 1 mg/1 g

Posatex® Otic Suspension
(Orbifloxacin, Mometasone Furoate Monohydrate and Posaconazole, Suspension)

Antibacterial, anti-inflammatory, antifungal

For Otic Use in Dogs Only

CAUTION: Federal law restricts this drug to use by or on the order of a licensed veterinarian.

Federal law prohibits the extralabel use of this drug in food-producing animals.

DESCRIPTION

DESCRIPTION: Each gram of POSATEX® Otic Suspension contains 10 mg of orbifloxacin; mometasone furoate monohydrate equivalent to 1 mg mometasone furoate; and 1 mg of posaconazole in a mineral oil based system containing a plasticized hydrocarbon gel.

Four drops of POSATEX® Otic Suspension delivers approximately 1.0 mg orbifloxacin, 0.1 mg of mometasone furoate monohydrate, and 0.1 mg of posaconazole.

VETERINARY INDICATIONS

INDICATIONS: POSATEX® Otic Suspension is indicated for the treatment of otitis externa in dogs associated with susceptible strains of yeast (Malassezia pachydermatis) and bacteria (coagulase positive staphylococci, Pseudomonas aeruginosa, and Enterococcus faecalis).

DOSAGE AND ADMINISTRATION: Shake well before use. For dogs weighing less than 30 lbs. instill 4 drops of POSATEX® Otic Suspension once daily into the ear canal. For dogs weighing 30 lbs. or more, instill 8 drops once daily into the ear canal. Therapy should continue for 7 consecutive days.

CONTRAINDICATIONS

CONTRAINDICATIONS: POSATEX® Otic Suspension is contraindicated in dogs with known or suspected hypersensitivity to quinolones, mometasone furoate monohydrate, or posaconazole. Do not use in dogs with known tympanic perforation (see PRECAUTIONS).

WARNINGS:

Human Warnings: Not for use in humans. Keep out of reach of children.

Animal Warnings: Do not administer orally. Immediately discontinue use of POSATEX® Otic Suspension if hearing loss is observed during treatment (see ADVERSE REACTIONS).

PRECAUTIONS

PRECAUTIONS: The use of POSATEX® Otic Suspension in dogs with perforated tympanic membranes has not been evaluated. The integrity of the tympanic membranes should be confirmed before administering this product.

Avoid prolonged or repeated use of POSATEX® Otic Suspension. Long-term use of topical otic corticosteroids has been associated with adrenocortical suppression and iatrogenic hyperadrenocorticism in dogs (see ANIMAL SAFETY).

The safe use of POSATEX® Otic Suspension in dogs used for breeding purposes, during pregnancy or in lactating bitches, has not been evaluated. The systemic administration of quinolones has been shown to produce cartilage erosions of weight bearing joints and other signs of arthropathy in immature animals of various species.

ADVERSE REACTIONS

ADVERSE REACTIONS: In the field study, 143 dogs were treated with POSATEX® Otic Suspension. Of those, 1 dog with bilateral otitis externa developed hearing loss. POSATEX® Otic Suspension treatment was discontinued and the condition resolved after one week.

To report suspected adverse reactions, call 1-800-224-5318.

For a copy of the Material Safety Data Sheet (MSDS) call 1-800-770-8878.

CLINICAL PHARMACOLOGY:

Orbifloxacin: Orbifloxacin is a synthetic fluoroquinolone antibacterial agent. The bactericidal action of fluoroquinolones is concentration-dependent and results from interference with bacterial DNA gyrase and topoisomerase IV. Since these enzymes are needed for bacterial DNA synthesis and transcription, fluoroquinolones disrupt bacterial replication and lead to bacterial cell death.

Mometasone: Mometasone furoate monohydrate is a topical corticosteroid characterized by a (2') furoate 17-ester having chlorine at the 9 and 21 positions.

Posaconazole: Posaconazole is a broad-spectrum triazole antifungal agent. The mechanism by which triazoles exert fungicidal action involves the selective inhibition of the enzyme lanosterol a C14 demethylase (a microsomal cytochrome P-450- dependent enzyme) involved in ergosterol biosynthesis in yeasts and filamentous fungi.

Systemic absorption of the active ingredients was determined in single-dose radiolabelled studies with ^14C-orbifloxacin, ^3H-mometasone furoate, and ^14C-posaconazole contained within the POSATEX® Otic Suspension formulation and placed into the ear canals of normal beagle dogs. Most of the absorption occurred in the first few days after administration. The extent of percutaneous absorption of topical medications is influenced by many factors including the integrity of the epidermal barrier. Inflammation can increase the percutaneous absorption of drugs.

EFFECTIVENESS: The effectiveness of POSATEX® Otic Suspension was evaluated in a placebo-controlled, double-blind, multi-site field study. One hundred and ninety one dogs with naturally occurring clinical otitis externa associated with both yeast and bacteria were randomly allocated to either POSATEX® Otic Suspension or placebo ointment. Of the 160 dogs evaluated for effectiveness, 122 were treated with POSATEX® Otic Suspension and 38 were treated with placebo ointment. Treatments were administered once daily for 7 consecutive days. Assessment of effectiveness was based on improvement in clinical signs at re-evaluation 2-7 days following administration of the last dose.

Compared to the placebo, a significant percent of dogs treated with POSATEX® Otic Suspension showed improvement in clinical signs (discomfort, erythema, and swelling) caused by otitis externa associated with one or more of the following organisms: Malassezia pachydermatis, coagulase positive staphylococci, Pseudomonas aeruginosa, and Enterococcus faecalis.

Percent of Dogs Showing Improvement in Clinical Signs of Otitis Externa
Clinical Sign | POSATEX® Otic Suspension Group | Placebo Group | Significance
Discomfort | 88% | 45% | p<0.0001
External Ear Canal Erythema | 81% | 39% | p<0.0001
External Ear Canal Swelling | 83% | 49% | p=0.0001

ANIMAL PHARMACOLOGY AND OR TOXICOLOGY

ANIMAL SAFETY: POSATEX® Otic Suspension was administered at 1,3, and 5 times the recommended dosage for 21 consecutive days. The control group received the vehicle in both ears at the clinical dose given five times per day. There was a slight decrease in serum cortisol concentration after ACTH stimulation on Day 21 in the 5× group. Erythema was noted in all groups. Aural pain, swelling, or heat were each noted in 3 separate dogs in the 5× group.

STORAGE AND HANDLING

STORAGE INFORMATION: Store at temperatures between 2°-30°C (35.6°-86°F).

Shake well before use.

HOW SUPPLIED

HOW SUPPLIED: POSATEX® Otic Suspension is available in 7.5 g, 15 g, and 30 g plastic bottles.

Approved by FDA under NADA # 141-266
Copyright© 2009, 2019 Intervet Inc., a subsidiary of Merck & Co. Inc.
Madison, NJ 07940 USA
All rights reserved.
Made in Germany
Rev. 02/2019

PRINCIPAL DISPLAY PANEL - 30 g Bottle Label

Posatex®
Otic Suspension
(orbifloxacin, mometasone
furoate monohydrate and
posaconazole suspension)

Antibacterial,
Anti-inflammatory,
Antifungal

Caution: Federal law
restricts this drug to use by
or on the order of a licensed
veterinarian.

Federal law prohibits the
extralabel use of this drug
in food-producing animals.

KEEP OUT OF REACH
OF CHILDREN.

Approved by FDA under NADA # 141-266
NDC 0061-0089-03

30g

MERCK
Animal Health